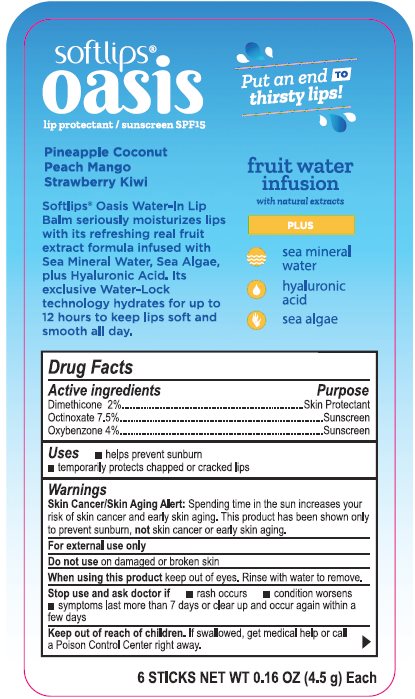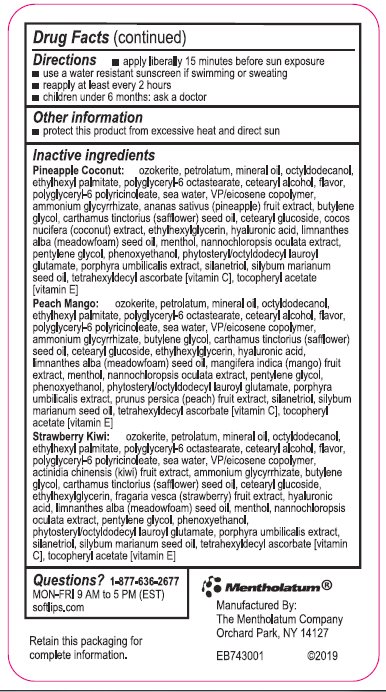 DRUG LABEL: Softlips
NDC: 10742-8744 | Form: STICK
Manufacturer: The Mentholatum Company
Category: otc | Type: HUMAN OTC DRUG LABEL
Date: 20241217

ACTIVE INGREDIENTS: DIMETHICONE 20 mg/1 g; OCTINOXATE 75 mg/1 g; OXYBENZONE 40 mg/1 g
INACTIVE INGREDIENTS: CERESIN; PETROLATUM; MINERAL OIL; OCTYLDODECANOL; ETHYLHEXYL PALMITATE; POLYGLYCERYL-6 DISTEARATE; CETOSTEARYL ALCOHOL; POLYGLYCERYL-3 RICINOLEATE; SODIUM CHLORIDE; VINYLPYRROLIDONE/EICOSENE COPOLYMER; KIWI FRUIT; AMMONIUM GLYCYRRHIZATE; PINEAPPLE; BUTYLENE GLYCOL; SAFFLOWER OIL; CETEARYL GLUCOSIDE; COCONUT; ETHYLHEXYLGLYCERIN; ALPINE STRAWBERRY; HYALURONIC ACID; MEADOWFOAM SEED OIL; MANGO; RACEMENTHOL; PHYMATOLITHON CALCAREUM; PENTYLENE GLYCOL; PHENOXYETHANOL; PHYTOSTERYL/OCTYLDODECYL LAUROYL GLUTAMATE; PORPHYRA UMBILICALIS; PEACH; SILANETRIOL; SILYBUM MARIANUM SEED OIL; TETRAHEXYLDECYL ASCORBATE; .ALPHA.-TOCOPHEROL ACETATE

Drug Facts - Oasis Pineapple Coconut, Peach Mango, Strawberry Kiwi

Active ingredient

Dimethicone 2%

Octinoxate 7.5%

Oxybenzone 4%

Purpose

Dimethicone - Skin protectant

Octinoxate - Sunscreen

Oxybenzone – Sunscreen

Uses

- helps prevent sunburn
- temporarily protects chapped or cracked lips

Warnings

Skin Cancer/Skin Aging Alert: Spending time in the sun increases your risk of skin cancer and early skin aging. This product has been shown only to prevent sunburn, not skin cancer or early skin aging.

For external use only

Do not use

on damaged or broken skin

When using this product

keep out of eyes. Rinse with water to remove.

Stop use and ask a doctor if

- rash occurs
- condition worsens
- symptoms last more than 7 days or clear up and occur again within a few days

Keep Out of Reach of Children

If swallowed, get medical help or contact a Poison Control Center right away.

Directions

- apply liberally 15 minutes before sun exposure
- use a water resistant sunscreen if swimming or sweating
- reapply at least every 2 hours
- children under 6 months: ask a doctor

Other information

- protect this product from excessive heat and direct sun

Inactive ingredients

Pineapple Coconut: ozokerite, petrolatum, mineral oil, octyldodecanol, ethylhexyl palmitate, polyglyceryl-6 octastearate, cetearyl alcohol, flavor, polyglyceryl-6 polyricinoleate, sea water, VP/eicosene copolymer, ammonium glycyrrhizate, ananas sativus (pineapple) fruit extract, butylene glycol, carthamus tinctorius (safflower) seed oil, cetearyl glucoside, cocos nucifera (coconut) extract, ethylhexylglycerin, hyaluronic acid, limnanthes alba (meadowfoam) seed oil, menthol, nannochloropsis oculata extract, pentylene glycol, phenoxyethanol, phytosteryl/octyldodecyl lauroyl glutamate, porphyra umbilicalis extract, silanetriol, silybum marianum seed oil, tetrahexyldecyl ascorbate [vitamin C], tocopheryl acetate [vitamin E]

Peach Mango: ozokerite, petrolatum, mineral oil, octyldodecanol, ethylhexyl palmitate, polyglyceryl-6 octastearate, cetearyl alcohol, flavor, polyglyceryl-6 polyricinoleate, sea water, VP/eicosene copolymer, ammonium glycyrrhizate, butylene glycol, carthamus tinctorius (safflower) seed oil, cetearyl glucoside, ethylhexylglycerin, hyaluronic acid, limnanthes alba (meadowfoam) seed oil, mangifera indica (mango) fruit extract, menthol, nannochloropsis oculata extract, pentylene glycol, phenoxyethanol, phytosteryl/octyldodecyl lauroyl glutamate, porphyra umbilicalis extract, prunus persica (peach) fruit extract, silanetriol, silybum marianum seed oil, tetrahexyldecyl ascorbate [vitamin C], tocopheryl acetate [vitamin E]

Strawberry Kiwi: ozokerite, petrolatum, mineral oil, octyldodecanol, ethylhexyl palmitate, polyglyceryl-6 octastearate, cetearyl alcohol, flavor, polyglyceryl-6 polyricinoleate, sea water, VP/eicosene copolymer, actinidia chinesis (kiwi) fruit extract, ammonium glycyrrhizate, butylene glycol, carthamus tinctorius (safflower) seed oil, cetearyl glucoside, ethylhexylglycerin, fragaria vesca (strawberry) fruit extract, hyaluronic acid, limnanthes alba (meadowfoam) seed oil, menthol, nannochloropsis oculata extract, pentylene glycol, phenoxyethanol, phytosteryl/octyldodecyl lauroyl glutamate, porphyra umbilicalis extract, silanetriol, silybum marianum seed oil, tetrahexyldecyl ascorbate [vitamin C], tocopheryl acetate [vitamin E]

Questions? 1-877-636-2677

MON-FRI 9 AM to 5 PM (EST) softlips.com